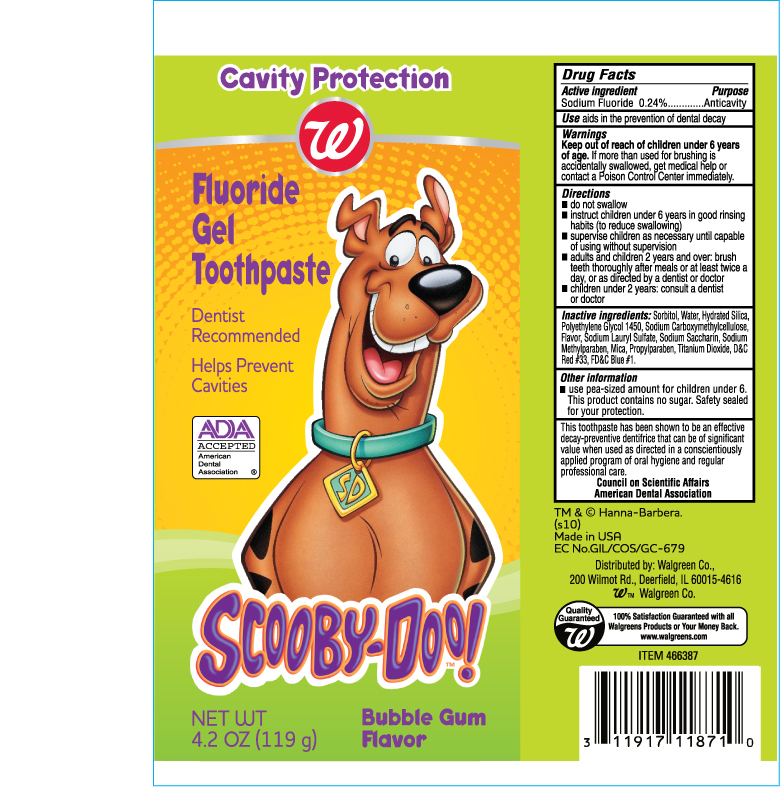 DRUG LABEL: Walgreens Scooby Doo Fluoride Gel Toothpaste
NDC: 67659-085 | Form: PASTE
Manufacturer: Team Technologies, Inc
Category: otc | Type: HUMAN OTC DRUG LABEL
Date: 20100726

ACTIVE INGREDIENTS: SODIUM FLUORIDE 2.4 mg/1 g
INACTIVE INGREDIENTS: SORBITOL; WATER; SILICON DIOXIDE; POLYETHYLENE GLYCOL 1450; CARBOXYMETHYLCELLULOSE SODIUM; SODIUM LAURYL SULFATE; SACCHARIN SODIUM; METHYLPARABEN SODIUM; PROPYLPARABEN; TITANIUM DIOXIDE; D&C RED NO. 33; FD&C BLUE NO. 1

Walgreens Cavity Protection Fluoride Gel Toothpaste

Active Ingredients

Sodium Fluoride 0.24% Anticavity

PURPOSE

Anticavity

WARNINGS

Keep out of reach of children under 6 years of age. If more than used for brushing is accidentally swallowed, get medical help or contact a Poison Control Center immediately.

Directions

- do not swallow
- instruct children under 6 years in good rinsing habits (to reduce swallowing)
- supervise children as necessary until capable of using with our supervision
- adults and children 2 years and over: brush teeth thoroughly after meals or at least twice a day, or as directed by a dentist or doctor
- children under 2 years: consult a dentist or doctor

Inactive ingredients

Sorbitol, Water, Hydrated Silica, Polyethylene Glycol 1450, Sodium Carboxymethylcellulose, Flavor, Sodium Lauryl Sulfate, Sodium Saccharin, Sodium Methylparaben, Mica, Propyparaben, Titanium Dioxide, D C Red 33, FD C Blue 1.

USE

Aids in the prevention of dental decay.

KEEP OUT OF REACH OF CHILDREN